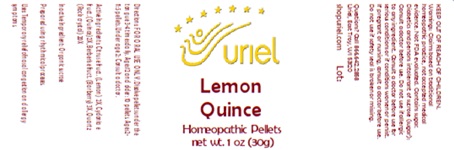 DRUG LABEL: Lemon Quince
NDC: 48951-6068 | Form: PELLET
Manufacturer: Uriel Pharmacy Inc
Category: homeopathic | Type: HUMAN OTC DRUG LABEL
Date: 20250122

ACTIVE INGREDIENTS: LEMON 2 [hp_X]/1 1; CHAENOMELES SINENSIS FRUIT 2 [hp_X]/1 1; BERBERIS VULGARIS FRUIT 3 [hp_X]/1 1; SILICON DIOXIDE 20 [hp_X]/1 1
INACTIVE INGREDIENTS: SUCROSE

Lemon Quince

INDICATIONS AND USAGE

Directions: FOR ORAL USE ONLY.

DOSAGE AND ADMINISTRATION

Dissolve pellets under the tongue 3-4 times daily. Ages 12 and older: 10 pellets. Ages 2-11: 5 pellets. Under age 2: Consult a doctor.

ACTIVE INGREDIENT

Active Ingredients: Citrus e fruct. (Lemon) 2X, Cydonia e fruct. (Quince) 2X, Berberis e fruct. (Barberry) 3X, Quartz (Rock crystal) 20X

Inactive Ingredient: Organic sucrose

Prepared using rhythmical processes.

PURPOSE

Uses: Temporary relief of nasal congestion and allergy symptoms.

KEEP OUT OF REACH OF CHILDREN.

WARNINGS

Warnings: Claims based on traditional homeopathic practice, not accepted medical evidence. Not FDA evaluated. Contains sugar. Diabetics and persons intolerant of sucrose (sugar): Consult a doctor before use. Do not use if allergic to any ingredient. Consult a doctor before use for serious conditions or if conditions worsen or persist. If pregnant or nursing, consult a doctor before use. Do not use if safety seal is broken or missing.

Questions? Call 866.642.2858
Uriel, East Troy, WI 53120
shopuriel.com